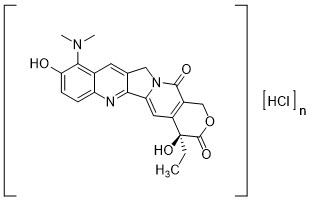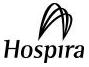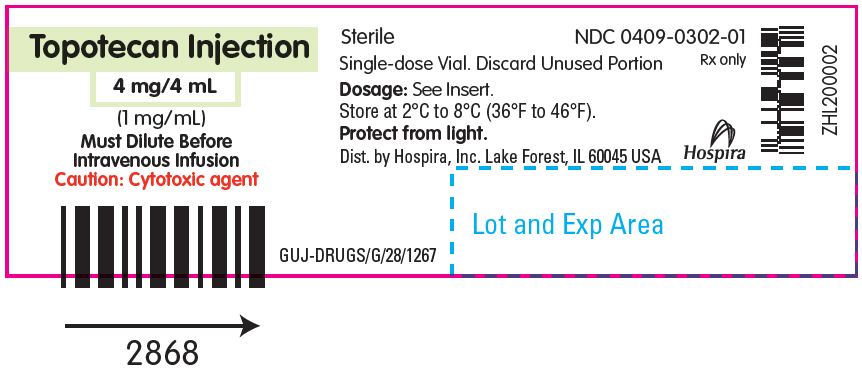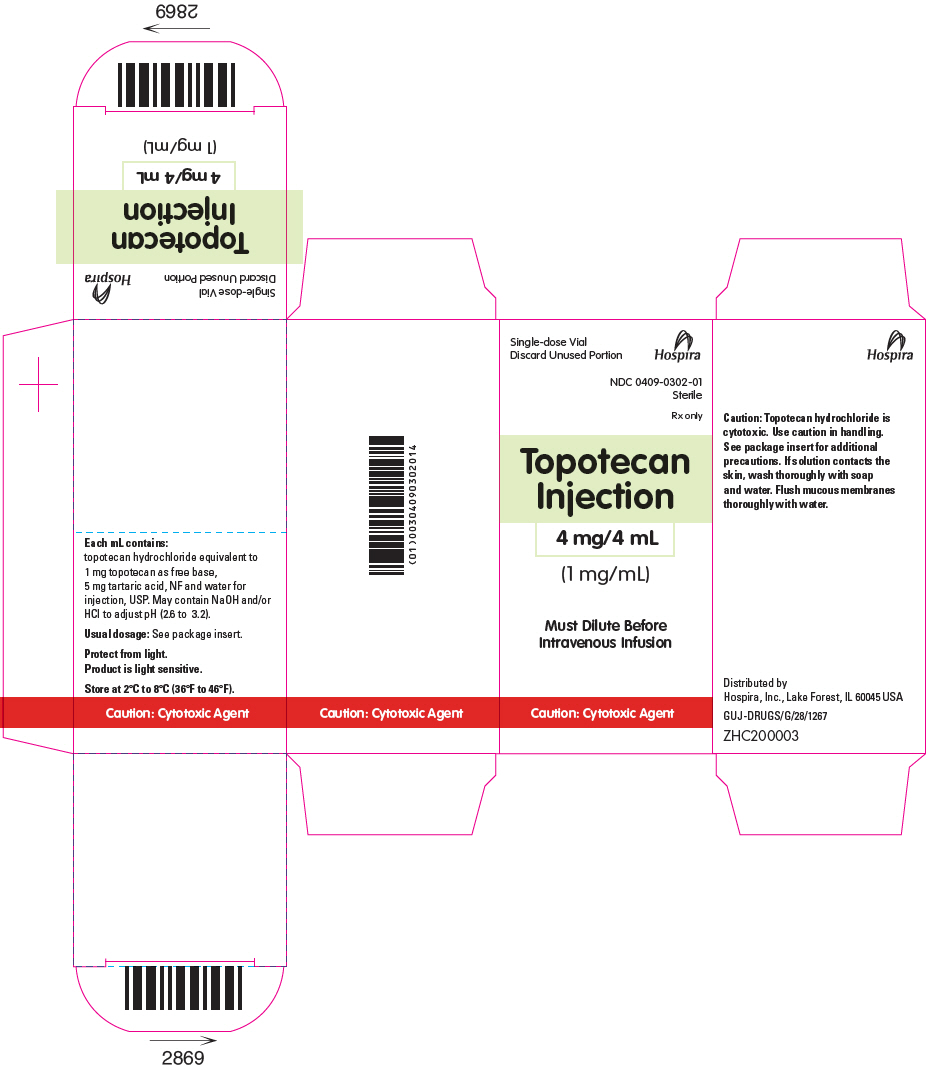 DRUG LABEL: Topotecan
NDC: 0409-0302 | Form: INJECTION, SOLUTION, CONCENTRATE
Manufacturer: Hospira, Inc.
Category: prescription | Type: HUMAN PRESCRIPTION DRUG LABEL
Date: 20210201

ACTIVE INGREDIENTS: TOPOTECAN HYDROCHLORIDE 1 mg/1 mL
INACTIVE INGREDIENTS: TARTARIC ACID 5 mg/1 mL; HYDROCHLORIC ACID; SODIUM HYDROXIDE; WATER

HIGHLIGHTS OF PRESCRIBING INFORMATION

These highlights do not include all the information needed to use TOPOTECAN INJECTION safely and effectively. See full prescribing information for TOPOTECAN INJECTION.
TOPOTECAN injection, for intravenous use
Initial U.S. Approval: 1996

WARNING: MYELOSUPPRESSION

See full prescribing information for complete boxed warning.

Topotecan can cause severe myelosuppression. Administer first cycle only to patients with baseline neutrophil counts greater than or equal to 1,500/mm^3 and platelet count greater than or equal to 100,000/mm^3. Monitor blood cell counts. (2.2, 5.1)

1 INDICATIONS AND USAGE

Topotecan Injection is a topoisomerase inhibitor indicated for treatment of small cell lung cancer (SCLC) platinum-sensitive disease in patients who progressed at least 60 days after initiation of first-line chemotherapy. (1)

2 DOSAGE AND ADMINISTRATION

- Recommended dosage: 1.5 mg/m^2 by intravenous infusion over 30 minutes daily for 5 consecutive days, starting on Day 1 of a 21-day cycle. (2.2)
- Renal impairment: Reduce dose for creatinine clearance (CLcr) of 20 to 39 mL/min. (2.4)

3 DOSAGE FORMS AND STRENGTHS

Injection: 4 mg/4 mL (1 mg/mL topotecan free base) solution in single-dose vial. (3)

4 CONTRAINDICATIONS

History of severe hypersensitivity reactions to topotecan. (4)

5 WARNINGS AND PRECAUTIONS

- Interstitial lung disease (ILD): Fatal cases have occurred. Permanently discontinue if ILD confirmed. (5.2)
- Extravasation and tissue injury: Severe cases have occurred. If extravasation occurs, immediately stop administration and institute recommended management procedures. (5.3)
- Embryo-fetal toxicity: Can cause fetal harm. Advise women of potential risk to the fetus. (5.4, 8.1, 8.3)

6 ADVERSE REACTIONS

- The most common Grade 3 or 4 hematologic adverse reactions (incidence >5%) were: neutropenia , anemia , thrombocytopenia, and febrile neutropenia. (6.1)
- The most common non-hematologic adverse reactions (incidence >5%) (all grades) were asthenia, dyspnea, nausea, pneumonia, abdominal pain, and fatigue. (6.1)

To report SUSPECTED ADVERSE REACTIONS, contact Hospira, Inc. at 1-800-441-4100 or FDA at 1-800-FDA-1088 or www.fda.gov/medwatch.

8 USE IN SPECIFIC POPULATIONS

Lactation: Advise not to breastfeed. (8.2)

FULL PRESCRIBING INFORMATION

WARNING: MYELOSUPPRESSION

Topotecan can cause severe myelosuppression. Administer first cycle only to patients with baseline neutrophil counts of greater than or equal to 1,500/mm^3and platelet counts greater than or equal to 100,000/mm^3. Monitor blood cell counts [see Warnings and Precautions (5.1)].

1 INDICATIONS AND USAGE

Topotecan Injection is indicated for the treatment of patients with small cell lung cancer (SCLC) with platinum-sensitive disease who progressed at least 60 days after initiation of first-line chemotherapy.

2 DOSAGE AND ADMINISTRATION

2.1 Important Safety Information

Verify dosage using body surface area. Do not exceed a single dose of 4 mg intravenously.

2.2 Recommended Dosage for Small Cell Lung Cancer

The recommended dosage of Topotecan Injection is 1.5 mg/m^2 by intravenous infusion over 30 minutes daily for 5 consecutive days, starting on Day 1 of a 21-day cycle.

2.3 Dosage Modifications for Adverse Reactions

Hematologic

Do not administer subsequent cycles of Topotecan Injection until neutrophils recover to greater than 1,000/mm^3, platelets recover to greater than 100,000/mm^3, and hemoglobin levels recover to greater than or equal to 9 g/dL (with transfusion if necessary).

Reduce the dose of Topotecan Injection to 1.25 mg/m^2/day for:

- neutrophil counts of less than 500/mm^3 or administer granulocyte-colony stimulating factor (G-CSF) starting no sooner than 24 hours following the last dose
- platelet counts less than 25,000/mm^3 during previous cycle

2.4 Dosage Modification for Renal Impairment

Reduce the dose of Topotecan Injection to 0.75 mg/m^2/day for patients with creatinine clearance (CLcr) of 20 to 39 mL/min (calculated with the Cockcroft-Gault method using ideal body weight) [see Clinical Pharmacology (12.3)].

2.5 Preparation and Administration

Topotecan Injection is a cytotoxic drug. Follow applicable special handling and disposable procedures.^1

Withdraw the appropriate volume from the vial and discard any unused portion.

Dilute Topotecan Injection in a minimum of 50 mL of 0.9% Sodium Chloride Injection, USP or 5% Dextrose Injection, USP prior to administration. Infuse diluted Topotecan Injection over 30 minutes.

Store diluted Topotecan Injection at 20°C and 25°C (68°F and 77°F) in ambient lighting conditions for no more than 24 hours. Discard unused portion after 24 hours.

Visually inspect for particulate matter and discoloration prior to administration, whenever solution and container permit. Discard if particulate matter or discoloration is observed.

3 DOSAGE FORMS AND STRENGTHS

Injection: 4 mg/4 mL (1 mg/mL topotecan free base) clear, yellow to yellow-green solution in single-dose vial.

4 CONTRAINDICATIONS

Topotecan Injection is contraindicated in patients who have a history of severe hypersensitivity reactions to topotecan. Reactions have included anaphylactoid reactions [see Adverse Reactions (6.2)].

5 WARNINGS AND PRECAUTIONS

5.1 Myelosuppression

Topotecan can cause severe myelosuppression.

Grade 4 neutropenia occurred in 78% of 879 patients, with a median duration of 7 days and was most common during Cycle 1 (58% of patients). Grade 4 neutropenia associated with infection occurred in 13% and febrile neutropenia occurred in 5%. Sepsis occurred in 4% and was fatal in 1%. Grade 4 thrombocytopenia occurred in 27%, with a median duration of 5 days. Grade 3 or 4 anemia occurred in 37% of patients.

Topotecan can cause fatal typhlitis (neutropenic enterocolitis). Consider the possibility of typhlitis in patients presenting with fever, neutropenia, and abdominal pain.

Administer the first cycle of Topotecan Injection only to patients with a baseline neutrophil count of greater than or equal to 1,500/mm^3 and a platelet count greater than or equal to 100,000/mm^3. Monitor blood counts frequently during treatment. Withhold and reduce dose of Topotecan Injection based on neutrophil counts, platelet counts and hemoglobin levels [see Dosage and Administration (2.3)].

5.2 Interstitial Lung Disease

Interstitial lung disease (ILD), including fatalities, has occurred with topotecan [see Adverse Reactions (6.2)]. Underlying risk factors include history of ILD, pulmonary fibrosis, lung cancer, thoracic radiation, and use of pneumotoxic drugs and/or colony stimulating factors. Monitor patients for pulmonary symptoms indicative of ILD (e.g., cough, fever, dyspnea, and/or hypoxia), and discontinue Topotecan Injection if a new diagnosis of ILD is confirmed.

5.3 Extravasation and Tissue Injury

Extravasation with topotecan has been observed; severe cases have been reported. If signs or symptoms of extravasation occur, immediately stop administration of Topotecan Injection and institute recommended management procedures [see Adverse Reactions (6.2)].

5.4 Embryo-Fetal Toxicity

Based on animal data, topotecan can cause fetal harm when administered to a pregnant woman. Topotecan caused embryolethality, fetotoxicity, and teratogenicity in rats and rabbits when administered during organogenesis. Advise women of the potential risk to a fetus. Advise females of reproductive potential to use effective contraception during treatment and for 6 months after the last dose of Topotecan Injection. Advise males with a female partner of reproductive potential to use effective contraception during treatment with Topotecan Injection and for 3 months after the last dose [see Use in Specific Populations (8.1, 8.3), Nonclinical Toxicology (13.1)].

6 ADVERSE REACTIONS

The following serious adverse reactions are described elsewhere in the labeling:

- Myelosuppression [see Warnings and Precautions (5.1)]
- Interstitial Lung Disease [see Warnings and Precautions (5.2)]
- Extravasation and Tissue Injury [see Warnings and Precautions (5.3)]

6.1 Clinical Trials Experience

Because clinical trials are conducted under widely varying conditions, adverse reaction rates observed in the clinical trials of a drug cannot be directly compared with rates in the clinical trials of another drug and may not reflect the rates observed in practice.

The data in Warnings and Precautions reflect exposure to topotecan from 8 trials in which 879 patients with small cell lung cancer (SCLC) and other solid tumors received topotecan 1.5 mg/m^2 by intravenous infusion daily for 5 consecutive days, starting on Day 1 of a 21-day cycle.

Small Cell Lung Cancer (SCLC)

The safety of topotecan was evaluated in randomized, comparative trial in patients with recurrent or progressive SCLC (Study 090) [see Clinical Studies (14.1)]. Table 1 shows the Grade 3 or 4 hematologic and non-hematologic adverse reactions in patients with SCLC.

Table 1. Adverse Reactions Occurring in ≥5% of Patients with Small Cell Lung Cancer in Study 090
Adverse Reactions | Topotecan (n = 107) | CAV [CAV = cyclophosphamide, doxorubicin and vincristine.] (n = 104)
Adverse Reactions | Grade 3–4 (%) | Grade 3–4 (%)
Hematologic
Grade 4 neutropenia (< 500/mm^3) | 70 | 72
Grade 3 or 4 anemia (Hgb < 8 g/dL) | 42 | 20
Grade 4 thrombocytopenia (< 25,000/mm^3) | 29 | 5
Febrile neutropenia | 28 | 26
Non-Hematologic
Respiratory, thoracic, and mediastinal
Dyspnea | 9 | 14
Pneumonia | 8 | 6
General and administrative site conditions
Asthenia | 9 | 7
Fatigue | 6 | 10
Pain [Pain includes body pain, skeletal pain, and back pain.] | 5 | 7
Gastrointestinal
Nausea | 8 | 6
Abdominal pain | 6 | 4
Infections
Sepsis [Death related to sepsis occurred in 3% of patients receiving topotecan and 1% of patients receiving CAV.] | 5 | 5

Hepatobiliary Disorders

Based on 879 patients with small cell lung cancer or another solid tumor who were treated with topotecan, Grade 3 or 4 elevated aspartate (AST) or alanine transaminase (ALT) occurred in 4% and Grade 3 or 4 elevated bilirubin occurred in less than 2% of patients.

6.2 Postmarketing Experience

The following reactions have been identified during postapproval use of topotecan. Because these reactions are reported voluntarily from a population of unknown size, it is not always possible to reliably estimate their frequency or establish a causal relationship to drug exposure.

Blood and Lymphatic System

Severe bleeding (in association with thrombocytopenia)

Hypersensitivity

Allergic manifestations, anaphylactoid reactions, angioedema

Gastrointestinal

Abdominal pain potentially associated with neutropenic enterocolitis, gastrointestinal perforation

Pulmonary

Interstitial lung disease

Skin and Subcutaneous Tissue

Severe dermatitis, severe pruritus

General and Administration Site Conditions

Extravasation, mucosal inflammation

8 USE IN SPECIFIC POPULATIONS

8.1 Pregnancy

Risk Summary

Based on animal data and its mechanism of action, Topotecan Injection can cause fetal harm when administered to a pregnant woman. There are no available clinical data on the use of topotecan in pregnancy. Topotecan caused embryolethality, fetotoxicity, and teratogenicity in rats and rabbits when administered during organogenesis at doses similar to the clinical dose (see Data). Advise pregnant women of the potential risk to a fetus.

In the U.S. general population, the background risk of major birth defects is 2% to 4% and of miscarriage is 15% to 20% of clinically recognized pregnancies.

Data

Animal Data

In rabbits, an intravenous dose of 0.10 mg/kg/day [(about equal to the 1.5 mg/m^2 clinical dose based on body surface area (BSA)] given on Days 6 through 20 of gestation caused maternal toxicity, embryolethality, and reduced fetal body weight. In the rat, an intravenous dose of 0.23 mg/kg/day (about equal to the 1.5 mg/m^2 clinical dose based on BSA) given for 14 days before mating through gestation Day 6 caused fetal resorption, microphthalmia, pre-implant loss, and mild maternal toxicity. Administration of an intravenous dose of 0.10 mg/kg/day (about half the 1.5 mg/m^2 clinical dose based on BSA) given to rats on Days 6 through 17 of gestation caused an increase in post-implantation mortality. This dose also caused an increase in total fetal malformations. The most frequent malformations were of the eye (microphthalmia, anophthalmia, rosette formation of the retina, coloboma of the retina, ectopic orbit), brain (dilated lateral and third ventricles), skull, and vertebrae.

8.2 Lactation

Risk Summary

There are no data on the presence of topotecan or its metabolites in human milk or their effects on the breastfed infant or on milk production. Lactating rats excrete high concentrations of topotecan in milk (see Data). Because of the potential for serious adverse reactions in breastfed infants, advise women not to breastfeed during treatment with Topotecan Injection and for 1 week after the last dose.

Data

Following intravenous administration of topotecan to lactating rats at a dose of 4.72 mg/m^2 (about twice the 1.5 mg/m^2 clinical dose based on BSA), topotecan was excreted into milk at concentrations up to 48-fold higher than those in plasma.

8.3 Females and Males of Reproductive Potential

Pregnancy Testing

Verify pregnancy status of females of reproductive potential prior to initiating Topotecan Injection [see Use in Specific Populations (8.1)].

Contraception

Topotecan can cause fetal harm when administered to a pregnant woman [see Use in Specific Populations (8.1)].

Females

Advise female patients of reproductive potential to use effective contraception during treatment with Topotecan Injection and for 6 months after the last dose.

Males

Topotecan may damage spermatozoa, resulting in possible genetic and fetal abnormalities. Advise males with a female partner of reproductive potential to use effective contraception during treatment with Topotecan Injection and for 3 months after the last dose [see Nonclinical Toxicology (13.1)].

Infertility

Females

Topotecan may have both acute and long-term effects on fertility [see Nonclinical Toxicology (13.1)].

Males

Effects on spermatogenesis occurred in animals administered topotecan [see Nonclinical Toxicology (13.1)].

8.4 Pediatric Use

Safety and effectiveness in pediatric patients have not been established.

8.5 Geriatric Use

Of the 879 patients with SCLC or another solid tumor who received topotecan in clinical trials, 32% were aged 65 years and older, while 3.8% were aged 75 years and older. No overall differences in effectiveness or safety were observed between these patients and younger patients and other reported clinical experience has not identified differences in responses between the elderly and younger patients.

8.6 Renal Impairment

Reduce the dose of Topotecan Injection for patients with a CLcr of 20 to 39 mL/min [see Dosage and Administration (2.4), Clinical Pharmacology (12.3)]. No dosage adjustment is recommended for patients with CLcr greater than or equal to 40 mL/min. Insufficient data are available in patients with CLcr less than 20 mL/min to provide a dosage recommendation for Topotecan Injection.

10 OVERDOSAGE

Overdoses (up to 10-fold of the recommended dose) have occurred in patients receiving intravenous topotecan. The primary complication of overdosage is myelosuppression. Elevated hepatic enzymes, mucositis, gastrointestinal toxicity and skin toxicity have occurred with overdosages. If an overdose is suspected, monitor the patient closely for myelosuppression and institute supportive-care measures as appropriate.

11 DESCRIPTION

Topotecan is a semi-synthetic derivative of camptothecin and a topoisomerase inhibitor. The chemical name for topotecan hydrochloride is (S)-10-[(dimethylamino)methyl]-4-ethyl-4,9-dihydroxy-1H-pyrano[3',4':6,7]indolizino[1,2-b]quinoline-3,14-(4H,12H)-dione 1.25 hydrochloride. It has the molecular formula C23H23N3O5∙xHCl (x=1.25) and a molecular weight of 467.02. It is soluble in water and melts with decomposition at 213°C to 218°C.

Topotecan hydrochloride has the following structural formula:

Topotecan Injection for intravenous use is supplied as a sterile, non-pyrogenic, clear, yellow to yellow-green solution in single-dose vial at a topotecan free base concentration of 4 mg/4 mL (1 mg/mL).

Each mL contains 1 mg topotecan free base (equivalent to 1.11 mg of topotecan hydrochloride), 5 mg tartaric acid, NF and water for injection, USP. It may also contain hydrochloric acid and/or sodium hydroxide to adjust the pH. The solution pH ranges from 2.6 to 3.2.

12 CLINICAL PHARMACOLOGY

12.1 Mechanism of Action

Topoisomerase I relieves torsional strain in DNA by inducing reversible single-strand breaks. Topotecan binds to the topoisomerase I-DNA complex and prevents re-ligation of these single-strand breaks. The cytotoxicity of topotecan is thought to be due to double-strand DNA damage produced during DNA synthesis, when replication enzymes interact with the ternary complex formed by topotecan, topoisomerase I, and DNA. Mammalian cells cannot efficiently repair these double-strand breaks.

12.3 Pharmacokinetics

Following administration of topotecan at doses of 0.5 to 1.5 mg/m^2 (0.3 to 1 times the recommended dose) administered as a 30-minute infusion, area under the curve (AUC) increases approximately proportional with dose.

Distribution

Protein binding of topotecan is approximately 35%.

Elimination

The terminal half-life of topotecan is 2 to 3 hours following intravenous administration.

Metabolism

Topotecan undergoes a reversible pH-dependent hydrolysis of its pharmacologically active lactone moiety. At pH ≤ 4, the lactone is exclusively present, whereas the ring-opened hydroxy-acid form predominates at physiologic pH. Topotecan is metabolized to an N-demethylated metabolite in vitro. The mean metabolite: parent AUC ratio was about 3% for total topotecan and topotecan lactone following intravenous administration.

Excretion

The overall recovery of total topotecan and its N-desmethyl metabolite in urine and feces over 9 days averaged 73% ± 2% following an intravenous dose. Mean values of 51% ± 3% as total topotecan and 3% ± 1% as N-desmethyl topotecan were excreted in the urine. Fecal elimination of total topotecan accounted for 18% ± 4% while fecal elimination of N-desmethyl topotecan was 1.7% ± 0.6%. An O-glucuronidation metabolite of topotecan and N-desmethyl topotecan has been identified in the urine.

Specific Populations

No clinically significant differences in the pharmacokinetics of topotecan were observed based on age, sex, or hepatic impairment following intravenous administration.

Patients with Renal Impairment

Compared to patients with CLcr > 60 mL/min (calculated by the Cockcroft-Gault method using ideal body weight), plasma clearance of topotecan lactone decreased by 33% in patients with CLcr 40 to 60 mL/min and decreased by 65% in patients with CLcr 20 to 39 mL/min. The effect on topotecan pharmacokinetics in patients with CLcr < 20 mL/min is unknown [see Dosage and Administration (2.4)].

Drug Interaction Studies

Clinical Studies

No clinically significant changes in topotecan pharmacokinetics were observed when coadministered cisplatin.

No clinically significant changes in the pharmacokinetics of free platinum were observed in patients coadministered cisplatin with topotecan.

In Vitro Studies

Topotecan does not inhibit CYP1A2, CYP2A6, CYP2C8/9, CYP2C19, CYP2D6, CYP2E, CYP3A, or CYP4A or dihydropyrimidine dehydrogenase.

13 NONCLINICAL TOXICOLOGY

13.1 Carcinogenesis, Mutagenesis, Impairment of Fertility

Carcinogenicity testing of topotecan has not been performed. Topotecan is known to be genotoxic to mammalian cells and is a probable carcinogen. Topotecan was mutagenic to L5178Y mouse lymphoma cells and clastogenic to cultured human lymphocytes with and without metabolic activation. It was also clastogenic to mouse bone marrow. Topotecan did not cause mutations in bacterial cells.

Topotecan given to female rats prior to mating at an intravenous dose of 1.4 mg/m^2 (about equal to the 1.5 mg/m^2 clinical dose based on BSA) caused superovulation possibly related to inhibition of follicular atresia. This dose given to pregnant female rats also caused increased pre-implantation loss. A one month study in dogs given a daily intravenous topotecan dose of 0.4 mg/m^2 (about 0.25 times the 1.5 mg/m^2 clinical dose based on BSA) suggests that treatment may cause an increase in the incidence of multinucleated spermatogonial giant cells in the testes.

14 CLINICAL STUDIES

14.1 Small Cell Lung Cancer

The efficacy of topotecan was studied in 426 patients with recurrent or progressive SCLC in a randomized, comparative trial and in 3 single-arm trials.

Randomized Comparative Trial

In a randomized, comparative trial, 211 patients were randomized 1:1 to received topotecan (1.5 mg/m^2 once daily intravenously for 5 days starting on Day 1 of a 21-day cycle) or CAV (cyclophosphamide 1,000 mg/m^2, doxorubicin 45 mg/m^2, vincristine 2 mg administered sequentially on Day 1 of a 21-day cycle). All patients were considered sensitive to first-line chemotherapy (responders who then subsequently progressed greater than or equal to 60 days after completion of first-line therapy). A total of 77% of patients treated with topotecan and 79% of patients treated with CAV received platinum/etoposide with or without other agents as first-line chemotherapy. The efficacy outcome measures were overall response rate, response duration, time to progression and overall survival (OS).

The results of the trial did not show statistically significant improvements in response rates, response duration, time to progression, and OS as shown in Table 2.

Table 2. Efficacy Results in Patients with Small Cell Lung Cancer Sensitive to First-Line Chemotherapy in Study 090
Parameter | Topotecan (n = 107) |  | CAV [CAV = cyclophosphamide, doxorubicin and vincristine.] (n = 104)
Overall response rate (95% CI) | 24% (16% to 32%) |  | 18% (11% to 26%)
Complete response rate | 0% |  | 1%
Partial response rate | 24% |  | 17%
Response duration [The calculation for duration of response was based on the interval between first response and time to progression.] (months)
Median (95% CI) | 3.3 (3.0 to 4.1) |  | 3.5 (3.0 to 5.3)
Time to progression (months)
Median (95% CI) | 3.1 (2.6 to 4.1) |  | 2.8 (2.5 to 3.2)
Hazard ratio (95% CI) |  | 0.92 (0.69 to 1.22)
Overall survival (months)
Median (95% CI) | 5.8 (4.7 to 6.8) |  | 5.7 (5.0 to 7.0)
Hazard ratio (95% CI) |  | 1.04 (0.78 to 1.39)
Abbreviations: CI = confidence interval.

The median time to response was similar in both arms: topotecan 6 weeks (2.4 weeks to 3.6 months) versus CAV 6 weeks (5.1 weeks to 4.2 months).

Changes on a disease-related symptom scale are presented in Table 3. It should be noted that not all patients had all symptoms, nor did all patients respond to all questions. Each symptom was rated on a 4-category scale with an improvement defined as a change in 1 category from baseline sustained over 2 cycles. Limitations in interpretation of the rating scale and responses preclude formal statistical analysis.

Table 3. Symptom Improvement [Defined as improvement sustained over at least 2 cycles compared with baseline.] in Patients with Small Cell Lung Cancer in Study 090
Symptom | Topotecan (n = 107) |  | CAV [CAV = cyclophosphamide, doxorubicin and vincristine.] (n = 104)
Symptom | n [Number of patients with baseline and at least 1 post-baseline assessment.] | % | n | %
Shortness of breath | 68 | 28 | 61 | 7
Interference with daily activity | 67 | 27 | 63 | 11
Fatigue | 70 | 23 | 65 | 9
Hoarseness | 40 | 33 | 38 | 13
Cough | 69 | 25 | 61 | 15
Insomnia | 57 | 33 | 53 | 19
Anorexia | 56 | 32 | 57 | 16
Chest pain | 44 | 25 | 41 | 17
Hemoptysis | 15 | 27 | 12 | 33

Single-Arm Trials

Topotecan was also studied in 3 open-label, non-comparative trials (Studies 014, 092 and 053) in a total of 319 patients with recurrent or progressive SCLC after treatment with first-line chemotherapy. In all 3 trials, patients were stratified as either sensitive (responders who then subsequently progressed greater than or equal to 90 days after completion of first-line therapy) or refractory (no response to first-line chemotherapy or who responded to first-line therapy and then progressed within 90 days of completing first-line therapy). Response rates ranged from 11% to 31% for sensitive patients and 2% to 7% for refractory patients. Median time to progression and median survival were similar in all 3 trials and the comparative trial.

15 REFERENCES

1. "OSHA Hazardous Drugs." OSHA. http://www.osha.gov/SLTC/hazardousdrugs/index.html.

16 HOW SUPPLIED/STORAGE AND HANDLING

Topotecan Injection is supplied in 4 mg/4 mL (1 mg/mL topotecan free base) single-dose vials. Each vial contains 4 mL of the sterile, clear, yellow to yellow-green solution.

NDC 0409-0302-01 (Package of 1 single-dose vial)

STORAGE AND HANDLING

Store refrigerated between 2°C and 8°C (36°F and 46°F) in the original carton to protect from light. Discard unused portion.

Topotecan Injection is a cytotoxic drug. Follow applicable handling and disposal procedures.^1

17 PATIENT COUNSELING INFORMATION

Myelosuppression

Inform patients that topotecan decreases blood cell counts such as white blood cells, platelets, and red blood cells. Advise patients to notify their healthcare provider promptly for fever, other signs of infection, or bleeding [see Warnings and Precautions (5.1)].

Interstitial Lung Disease (ILD)

Inform patients of the risks of severe ILD. Advise patients to contact their healthcare provider immediately to report new or worsening respiratory symptoms [see Warnings and Precautions (5.2)].

Embryo-Fetal Toxicity

Advise females of reproductive potential and males with female partners of reproductive potential of the potential risk to a fetus. Advise women to contact their healthcare provider if they become pregnant, or if pregnancy is suspected during treatment with Topotecan Injection [see Warnings and Precautions (5.4), Use in Specific Populations (8.1, 8.3)].

Advise females of reproductive potential to use effective contraception during treatment with Topotecan Injection and for 6 months after the last dose [see Use in Specific Populations (8.1, 8.3)].

Advise males with a female sexual partner of reproductive potential to use effective contraception during treatment with Topotecan Injection and for 3 months after the last dose [see Use in Specific Populations (8.1, 8.3), Nonclinical Toxicology (13.1)].

Lactation

Advise women to discontinue breastfeeding during treatment with Topotecan Injection and for at least 1 week after the last dose [see Use in Specific Populations (8.2)].

Infertility

Advise male and female patients of the potential risk for impaired fertility [see Use in Specific Populations (8.3), Nonclinical Toxicology (13.1)].

Asthenia and Fatigue

Advise patients that topotecan may cause asthenia or fatigue. These symptoms may impair the ability to safely drive or operate machinery.

Distributed by Hospira, Inc., Lake Forest, IL 60045 USA

LAB-1355-2.0

PRINCIPAL DISPLAY PANEL - 4 mg/4 mL Vial Label

Topotecan Injection

4 mg/4 mL

(1 mg/mL)

Must Dilute Before
Intravenous Infusion

Caution: Cytotoxic agent

PRINCIPAL DISPLAY PANEL - 4 mg/4 mL Vial Carton

Single-dose Vial
Discard Unused Portion

Hospira

NDC 0409-0302-01
Sterile

Rx only

Topotecan
Injection

4 mg/4 mL

(1 mg/mL)

Must Dilute Before
Intravenous Infusion

Caution: Cytotoxic Agent